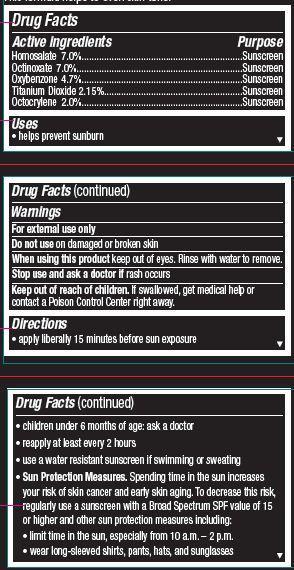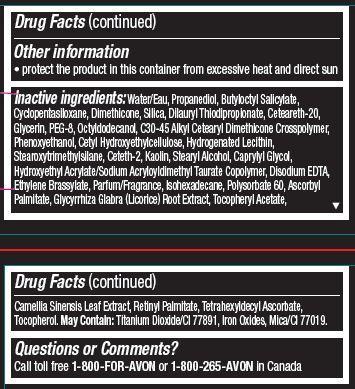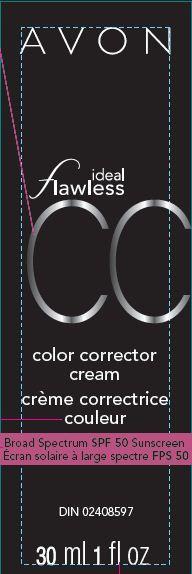 DRUG LABEL: Ideal Flawless
NDC: 10096-0307 | Form: CREAM
Manufacturer: New Avon LLC
Category: otc | Type: HUMAN OTC DRUG LABEL
Date: 20160219

ACTIVE INGREDIENTS: HOMOSALATE 70 mg/1 mL; OCTINOXATE 70 mg/1 mL; OXYBENZONE 47 mg/1 mL; TITANIUM DIOXIDE 21.5 mg/1 mL; OCTOCRYLENE 20 mg/1 mL

Active ingredient
Homosalate 7.0%.............................................
Octinoxate 7.0%.............................................
Oxybenzone 4.7%...........................................
Titanium Dioxide 2.15%..................................
Octocrylene 2.0%.............................................

Purpose
.................................Sunscreen

.................................Sunscreen

.................................Sunscreen

.................................Sunscreen

.................................Sunscreen

Uses
• helps prevent sunburn

Warnings
For external use only

Do not use on damaged or broken skin

When using this product keep out of eyes. Rinse with water to remove.

Stop use and ask a doctor if rash occurs

Keep out of reach of children. If swallowed, get medical help or contact a Poison Control Center right away.

Directions
• apply liberally 15 minutes before sun exposure
• children under 6 months of age: ask a doctor
• reapply at least every 2 hours
• use a water resistant sunscreen if swimming or sweating
• Sun Protection Measures. Spending time in the sun increases your risk of skin cancer and early skin aging. To decrease this risk, regularly use a sunscreen with a Broad Spectrum SPF value of 15 or higher and other sun protection measures including:
• limit time in the sun, especially from 10 a.m. – 2 p.m.
• wear long-sleeved shirts, pants, hats, and sunglasses

Other information

• protect the product in this container from excessive heat and direct sun

Inactive Ingredients:
Water/Eau, Propanediol, Butyloctyl Salicylate, Cyclopentasiloxane, Dimethicone, Silica, Dilauryl Thiodipropionate, Ceteareth-20, Glycerin, PEG-8, Octyldodecanol, C30-45 Alkyl Cetearyl Dimethicone Crosspolymer, Phenoxyethanol, Cetyl Hydroxyethylcellulose, Hydrogenated Lecithin, Stearoxytrimethylsilane, Ceteth-2, Kaolin, Stearyl Alcohol, Caprylyl Glycol, Hydroxyethyl Acrylate/Sodium Acryloyldimethyl Taurate Copolymer, Disodium EDTA, Ethylene Brassylate, Parfum/Fragrance, Isohexadecane, Polysorbate 60, Ascorbyl
Palmitate, Glycyrrhiza Glabra (Licorice) Root Extract, Tocopheryl Acetate, Camellia Sinensis Leaf Extract, Retinyl Palmitate, Tetrahexyldecyl Ascorbate, Tocopherol. May Contain: Titanium Dioxide/CI 77891, Iron Oxides, Mica/CI 77019.

Questions or Comments?
Call toll free 1-800-FOR-AVON or 1-800-265-AVON in Canada